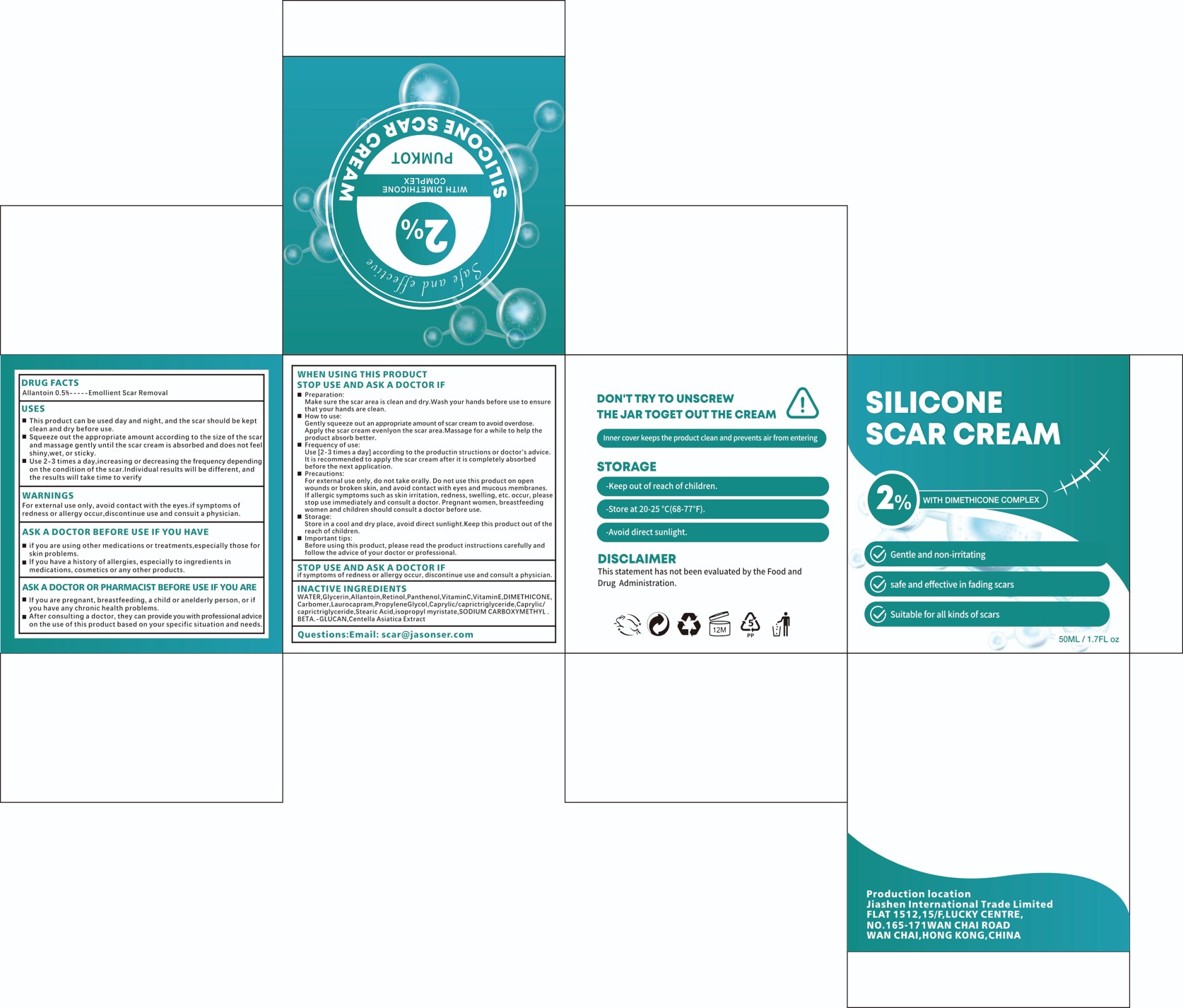 DRUG LABEL: pumkot SILICONE SCAR
NDC: 84867-006 | Form: CREAM
Manufacturer: Jiashen International Trade Limited
Category: otc | Type: HUMAN OTC DRUG LABEL
Date: 20241113

ACTIVE INGREDIENTS: ALLANTOIN 25 mg/50 mL
INACTIVE INGREDIENTS: PANTHENOL; WATER; CENTELLA ASIATICA TRITERPENOIDS; STEARIC ACID; ASCORBIC ACID; CAPRYLIC/CAPRIC TRIGLYCERIDE; DIMETHICONE; PROPYLENE GLYCOL; SODIUM CARBOXYMETHYL .BETA.-GLUCAN (DS 0.65-0.85); ISOPROPYL MYRISTATE; GLYCERIN; RETINOL; ALPHA-TOCOPHEROL; CARBOMER; LAUROCAPRAM

ACTIVE INGREDIENT

Allantoin:0.5%

INACTIVE INGREDIENT

WATER
Glycerin
Allantoin
Retinol
Panthenol
Vitamin C
Vitamin E
DIMETHICONE
Carbomer
Laurocapram
Propylene Glycol
Caprylic/capric triglyceride
Stearic Acid
Isopropyl myristate
SODIUM CARBOXYMETHYL .BETA.-GLUCAN
Centella Asiatica Extract

PURPOSE

Gentle and non-irritating
safe and effective in fading scars
Suitable for all kinds of scars

WARNINGS

For external use only, avoid contact with the eyes.if symptoms ofredness or allergy occur,discontinue use and consuit a physician.

STOP USE AND ASK A DOCTOR IF
if symptoms of redness or allergy occur, discontinue use and consult a physician.

DO NOT USE

Precautions:
For external use only, do not take orally. Do not use this product on openwounds or broken skin, and avoid contact with eyes and mucous membranes.If allergic symptoms such as skin irritation, redness, swelling, etc. occur, pleasestop use immediately and consult a doctor, Pregnant women, breastfeedingwomen and children should consult a doctor before use.

KEEP OUT OF REACH OF CHILDREN

Storage:Store in a cool and dry place, avoid direct sunlight.Keep this product out of thereach of children.

INDICATIONS AND USAGE

This product can be used day and night, and the scar should be keptclean and dry before use.
Squeeze out the appropriate amount according to the size of the scarand massage gently until the scar cream is absorbed and does not feelshiny,wet,or sticky.
Use 2-3 times a day,increasing or decreasing the frequency dependingon the condition of the scar.Individual results will be different, andthe results will take time to verify

DOSAGE AND ADMINISTRATION

Use [2-3 times a day] according to the productin structions or doctor's advice.It is recommended to apply the scar cream after it is completely absorbedbefore the next application.

WHEN USING

Preparation:Make sure the scar area is clean and dry.Wash your hands before use to ensurethat your hands are clean.How to use:Gently squeeze out an appropriate amount of scar cream to avoid overdose.Apply the scar cream evenlyon the scar area.Massage for a while to help theproduct absorb better.Frequency of use:Use [2-3 times a day] according to the productin structions or doctor's advice.It is recommended to apply the scar cream after it is completely absorbed
before the next application.Precautions:For external use only, do not take orally. Do not use this product on openwounds or broken skin, and avoid contact with eves and mucous membranes.If allergic symptoms such as skin irritation, redness, swelling, etc. occur, pleasestop use immediately and consult a doctor, Pregnant women, breastfeedingwomen and children should consult a doctor before use.Storage:
Store in a cool and dry place, avoid direct sunlight.Keep this product out of thereach of children.Important tips:Before using this product, please read the product instructions carefully andfollow the advice of your doctor or professional.